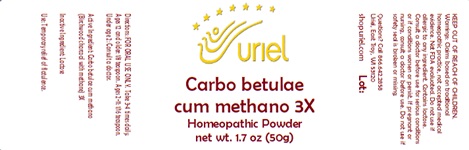 DRUG LABEL: Carbo betulae cum methano 3X
NDC: 48951-3259 | Form: POWDER
Manufacturer: Uriel Pharmacy Inc.
Category: homeopathic | Type: HUMAN OTC DRUG LABEL
Date: 20231204

ACTIVE INGREDIENTS: ACTIVATED CHARCOAL 3 [hp_X]/1 g
INACTIVE INGREDIENTS: LACTOSE

Carbo betulae cum methano 3X

INDICATIONS AND USAGE

Directions: FOR ORAL USE ONLY.

DOSAGE AND ADMINISTRATION

Take 3-4 times daily. Ages 12 and older: 1/8 teaspoon. Ages 2-11: 1/16 teaspoon. Under age 2: Consult a doctor.

Active Ingredient: Carbo betulae cum methano (Birchwood charcoal with methane) 3X

Inactive Ingredient: Lactose

PURPOSE

Use: Temporary relief of flatulence.

KEEP OUT OF REACH OF CHILDREN.

WARNINGS

Warnings: Claims based on traditional homeopathic practice, not accepted medical evidence. Not FDA evaluated. Do not use if allergic to any ingredient. Contains lactose. Consult a doctor before use for serious conditions or if conditions worsen or persist. If pregnant or nursing, consult a doctor before use. Do not use if safety seal is broken or missing.

QUESTIONS

Questions? Call 866.642.2858 Uriel, East Troy, WI 53120 shopuriel.com